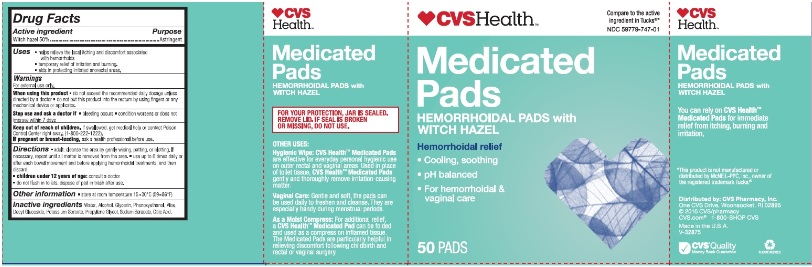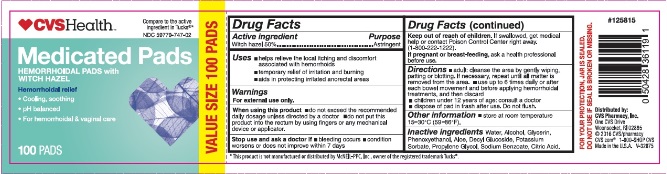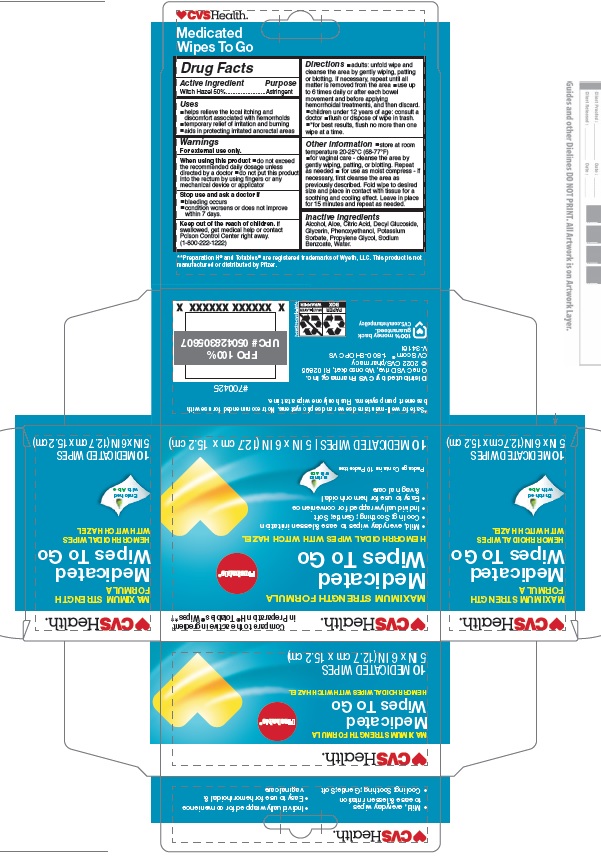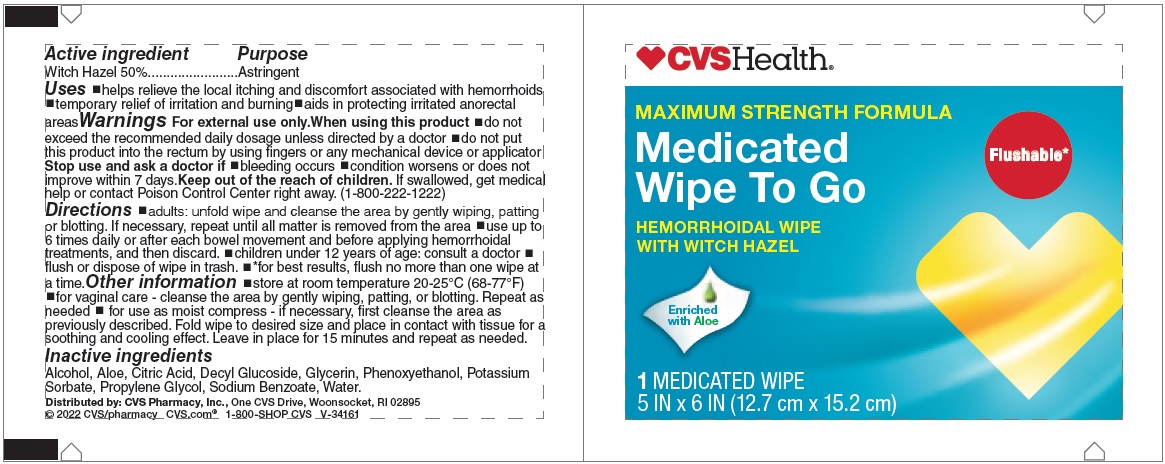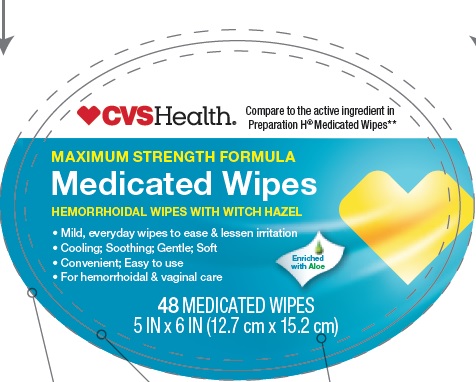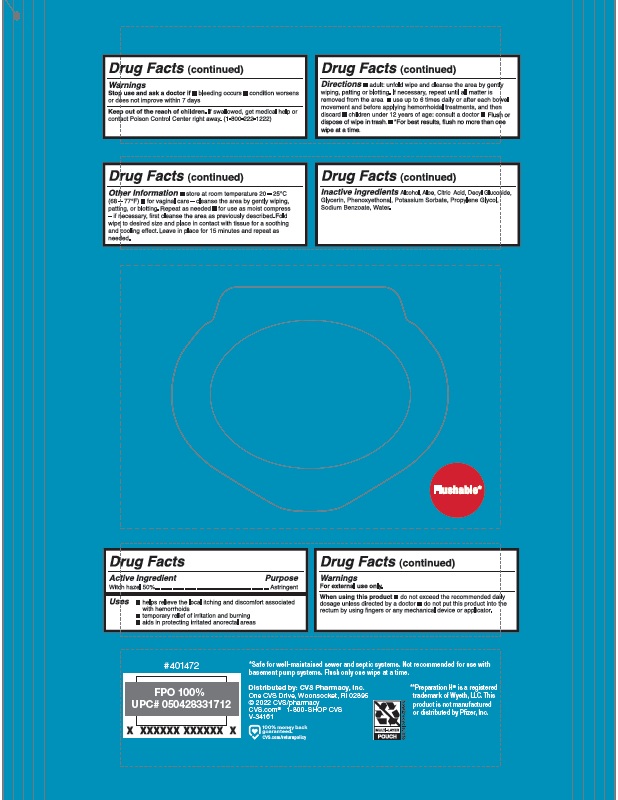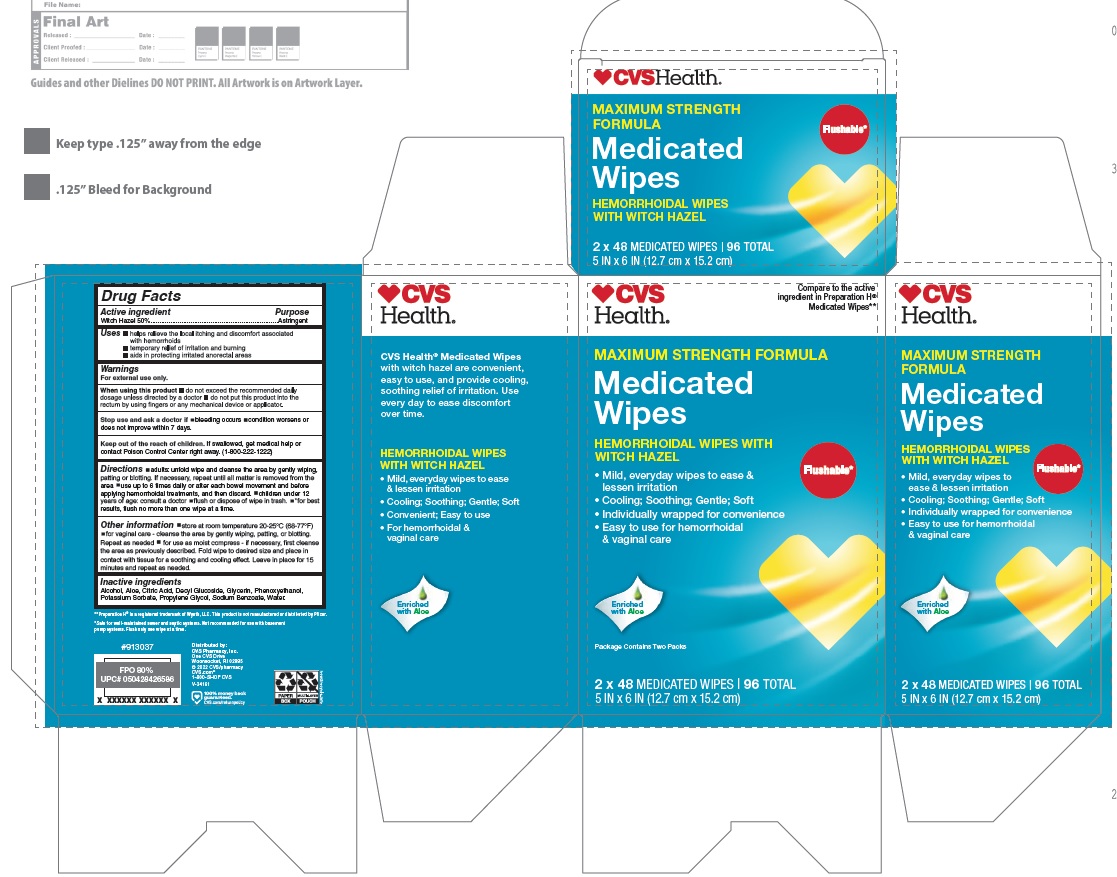 DRUG LABEL: CVS Health
NDC: 59779-747 | Form: CLOTH
Manufacturer: CVS Pharmacy
Category: otc | Type: HUMAN OTC DRUG LABEL
Date: 20251205

ACTIVE INGREDIENTS: WITCH HAZEL 500 mg/1 1
INACTIVE INGREDIENTS: WATER; ALCOHOL; GLYCERIN; PHENOXYETHANOL; ALOE; DECYL GLUCOSIDE; POTASSIUM SORBATE; PROPYLENE GLYCOL; SODIUM BENZOATE; CITRIC ACID MONOHYDRATE

Drug Facts

Active ingredient

Witch hazel 50%

Purpose

Astringent

Uses

- helps relieve the local itching and discomfort associated with hemorrhoids
- temporary relief of irritation and burning.
- aids in protecting irritated anorectal areas.

Warnings

For external use only.

When using this product

- do not exceed the recommended daily dosage unless directed by a doctor
- do not put this product into the rectum by using fingers or any mechanical device or applicator.

Stop use and ask a doctor if

- bleeding occurs
- condition worsens or does not improve within 7 days

Keep out of reach of children.

If swallowed, get medical help or contact Poison Control Center right away. (1-800-222-1222).

If pregnant or breast-feeding,

ask a health professional before use.

Directions

- adult: cleanse the area by gently wiping, patting or blotting. If necessary, repeat until all matter is removed from the area.
- use up to 6 times daily or after each bowel movement and before applying hemorrhoidal treatments, and then discard
- children under 12 years of age: consult a doctor
- do not flush in toilets, dispose of pad in trash after use.

Other information

- store at room temperature 15- 30oC (59 - 86oF)

Inactive ingredients

Water, Alcohol, Glycerin, Phenoxyethanol, Aloe, Decyl Glucoside, Potassium Sorbate, Propylene Glycol, Sodium Benzoate, Citric Acid.

Principal Display Panel

CVS Health

Compare to the active ingredient in Tucks®*

NDC 59779-747-01

Medicated Pads

HEMORRHOIDAL PADS with WITCH HAZEL

Hemorrhoidal relief

- Cooling, soothing
- pH balanced
- For hemorrhoidal and vaginal care

50 PADS

*This product is not manufactured or distributed by McNEIL-PPC, Inc, owner of the registered trademark Tucks®

CVS Health

Compare to the active ingredient in Tucks®*

NDC 59779-747-02

Medicated Pads

HEMORRHOIDAL PADS with WITCH HAZEL

Hemorrhoidal relief

- Cooling, soothing
- pH balanced
- For hemorrhoidal and vaginal care

100 PADS

VALUE SIZE 100 PADS

*This product is not manufactured or distributed by McNEIL-PPC, Inc, owner of the registered trademark Tucks®

CVS Health

MAXIMUM STRENGTH FORMULA

Medicated

Wipes To Go

HEMORRHOIDAL WIPES WITH WITCH HAZEL

- Mild, everyday wipes to ease & lessen irritation
- Cooling; Soothing; Gentle; Soft
- Individually wrapped for convenience
- Easy to use for hemorrhoidal & vaginal care

10 MEDICATED WIPES

CVSHealth

MAXIMUM STRENGTH FORMULA

Medicated Wipes

HEMORRHOIDAL WIPES WITH WITCH HAZEL

- Mild, everyday wipes to ease & lessen irritation
- Cooling: Soothing: Gentle: Soft
- Convenient: Easy to use
- For hemorrhoidal & vaginal care

48 MEDICATED WIPES

CVS Health

MAXIMUM STRENGTH FORMULA

Medicated

Wipes

HEMORRHOIDAL WIPES WITH WITCH HAZEL

- Mild, everyday wipes to ease & lessen irritation
- Cooling; Soothing; Gentle; Soft
- Individually wrapped for convenience
- Easy to use for hemorrhoidal & vaginal care

2 x 48 MEDICATED WIPES | 96 TOTAL

MAXIMUM STRENGTH FORMULA

Medicated Wipe To Go

HEMORRHOIDAL WIPE WITH WITCH HAZEL

1 MEDICATED WIPE